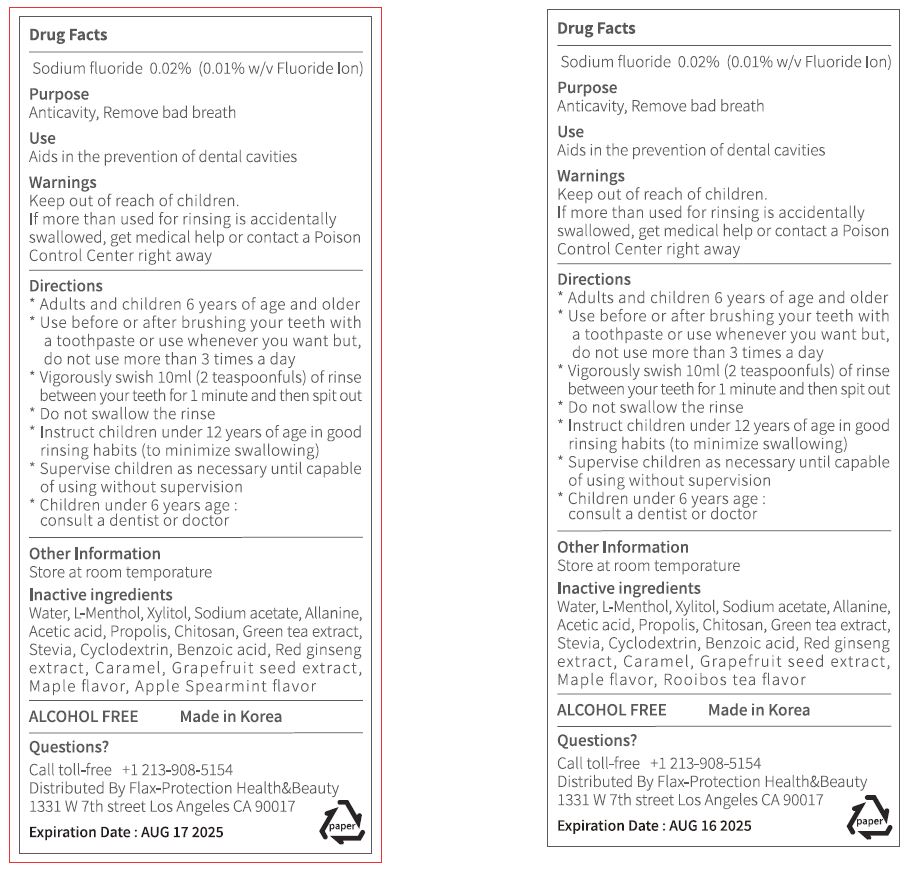 DRUG LABEL: Hoo gargle (Rooibos Tea Flavor)(Mouthwash)
NDC: 81840-2222 | Form: LIQUID
Manufacturer: MIKO CO LTD
Category: otc | Type: HUMAN OTC DRUG LABEL
Date: 20231006

ACTIVE INGREDIENTS: SODIUM FLUORIDE 0.02 g/100 mL
INACTIVE INGREDIENTS: WATER

Drug Facts

ACTIVE INGREDIENT

sodium fluoride

INACTIVE INGREDIENT

menthol

xylitol

Sodium acetate

Allanine
Acetic acid
Propolis
Chitosan
Green tea extract

Stevia
Cyclodextrin
Benzoic acid
Red ginsengs extract

Caramel
Grapefruit seed extract

Maple flavor
Rooibos tea flavor

Purified Water

PURPOSE

dental care

KEEP OUT OF REACH OF THE CHILDREN

INDICATIONS AND USAGE

1. Put one cup in mouth.

2. Gargle for 30 sec ~ 1 minute

3. Spit it out.

5. Rinse with water.

WARNINGS

Be careful not to swallow it, and rinse your mouth thoroughly after use.

DOSAGE AND ADMINISTRATION

dental use only